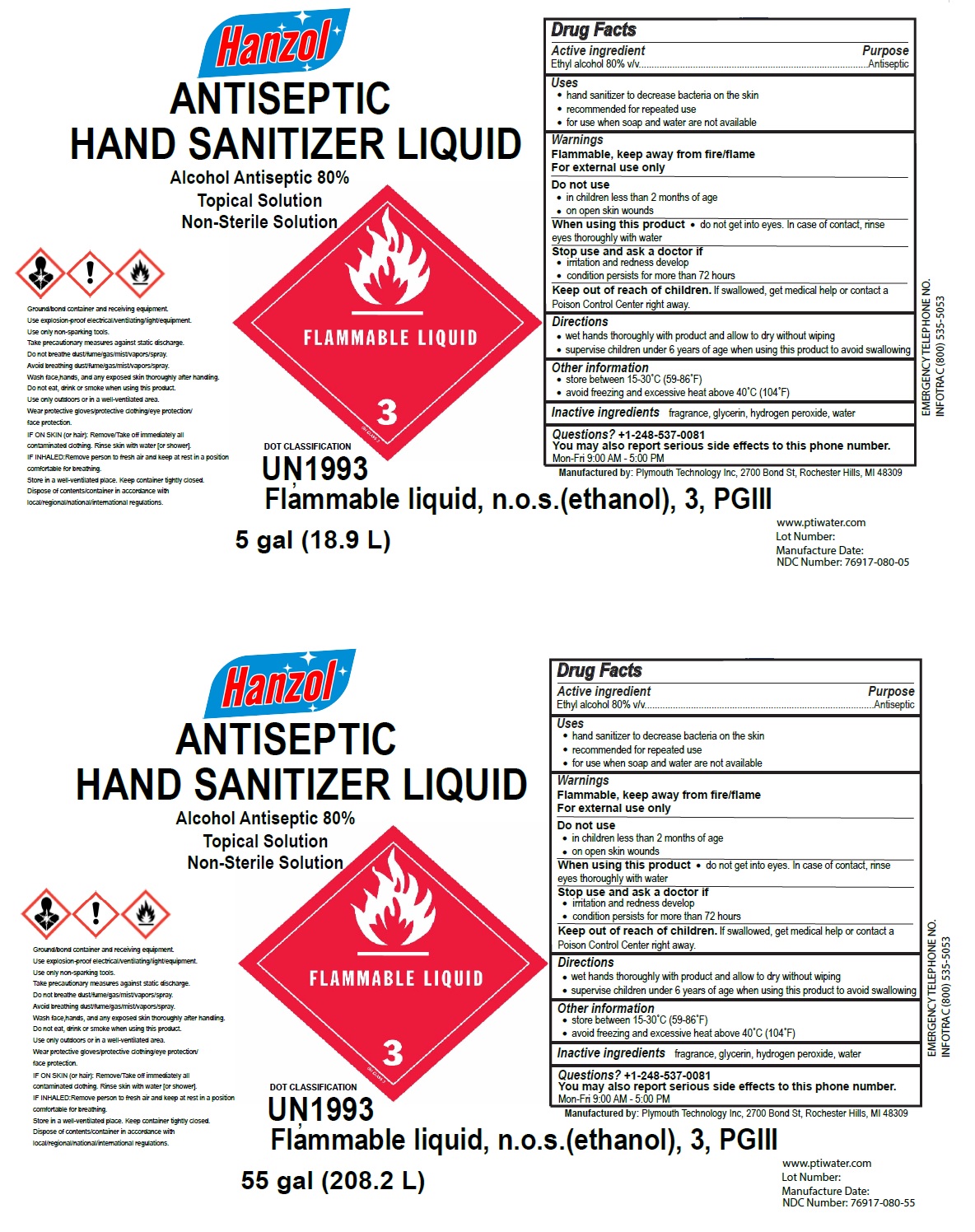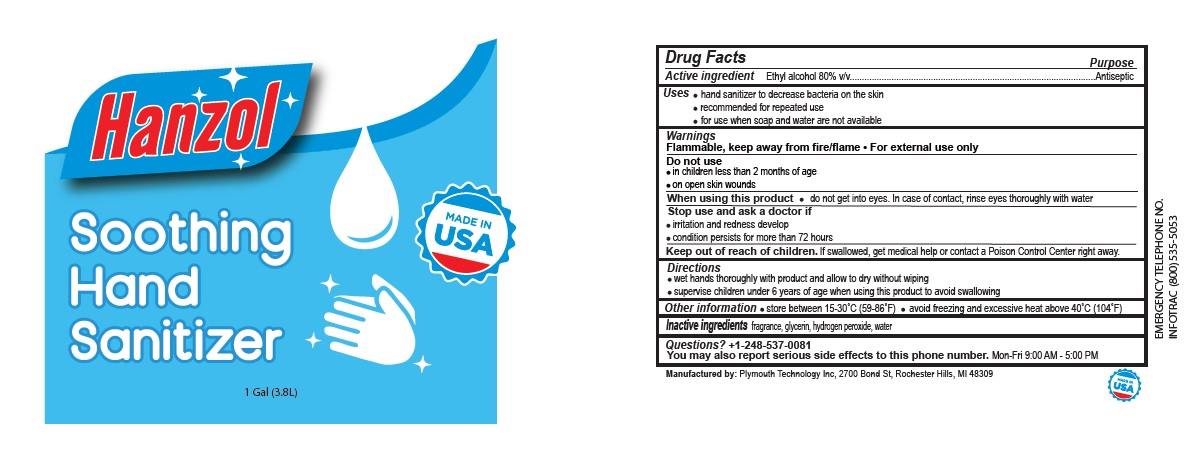 DRUG LABEL: Hanzol 
NDC: 76917-080 | Form: LIQUID
Manufacturer: Plymouth Technology, Inc
Category: otc | Type: HUMAN OTC DRUG LABEL
Date: 20200506

ACTIVE INGREDIENTS: ALCOHOL 80 L/100 L
INACTIVE INGREDIENTS: GLYCERIN; HYDROGEN PEROXIDE; WATER

Hanzol ANTISEPTIC HAND SANITIZER LIQUID

Active ingredient

Ethyl alcohol 80% v/v.

Purpose

Antiseptic

Uses

- hand sanitizer to decrease bacteria on the skin
- recommended for repeated use
- for use when soap and water are not available

Warnings

Flammable, keep away from fire/flame

For external use only

Do not use

- in children less than 2 months of age
- on open skin wounds

When using this product • do not get into eyes. In case of contact, rinse eyes thoroughly with water

Stop use and ask a doctor if

- irritation and redness develop
- condition persists for more than 72 hours

Keep out of reach of children. If swallowed, get medical help or contact a Poison Control Center right away.

Directions

- wet hands thoroughly with product and allow to dry without wiping
- supervise children under 6 years of age when using this product to avoid swallowing

Other information

- store between 15-30˚C (59-86˚F)
- avoid freezing and excessive heat above 40˚C (104˚F)

Inactive ingredients fragrance, glycerin, hydrogen peroxide, water

Alcohol Antiseptic 80%

Topical Solution

Non-Sterile Solution

DOT CLASSIFICATION

UN1993, Flammable liquid, n.o.s.(ethanol), 3, PGIII

Ground/bond container and receiving equipment. Use explosion-proof electrical/ventilating/light/equipment. Use only non-sparking tools. Take precautionary measures against static discharge. Do not breathe dust/fume/gas/mist/vapors/spray. Avoid breathing dust/fume/gas/mist/vapors/spray. Wash face,hands, and any exposed skin thoroughly after handling. Do not eat, drink or smoke when using this product. Use only outdoors or in a well-ventilated area. Wear protective gloves/protective clothing/eye protection/ face protection.

IF ON SKIN (or hair): Remove/Take off immediately all contaminated clothing. Rinse skin with water [or shower].

IF INHALED:Remove person to fresh air and keep at rest in a position comfortable for breathing.

Store in a well-ventilated place. Keep container tightly closed.

Dispose of contents/container in accordance with local/regional/national/international regulations.

Manufactured by: Plymouth Technology Inc, 2700 Bond St, Rochester Hills, MI 48309

www.ptiwater.com

EMERGENCY TELEPHONE NO.

INFOTRAC (800) 535-5053